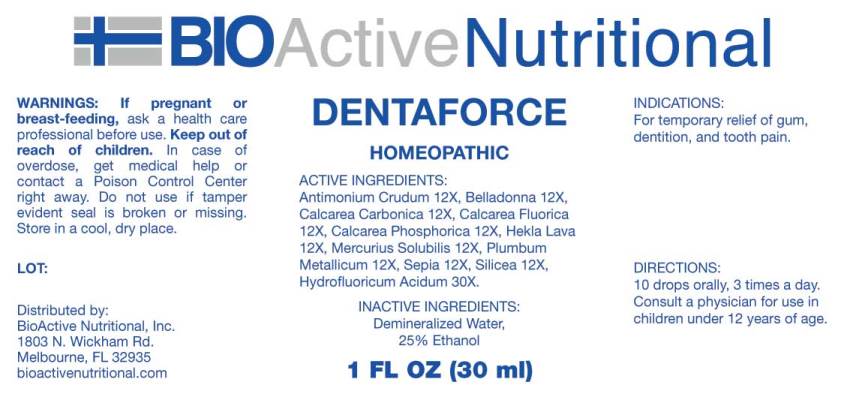 DRUG LABEL: Dentaforce
NDC: 43857-0093 | Form: LIQUID
Manufacturer: BioActive Nutritional, Inc.
Category: homeopathic | Type: HUMAN OTC DRUG LABEL
Date: 20170811

ACTIVE INGREDIENTS: ANTIMONY TRISULFIDE 12 [hp_X]/1 mL; ATROPA BELLADONNA 12 [hp_X]/1 mL; OYSTER SHELL CALCIUM CARBONATE, CRUDE 12 [hp_X]/1 mL; CALCIUM FLUORIDE 12 [hp_X]/1 mL; TRIBASIC CALCIUM PHOSPHATE 12 [hp_X]/1 mL; HEKLA LAVA 12 [hp_X]/1 mL; MERCURIUS SOLUBILIS 12 [hp_X]/1 mL; LEAD 12 [hp_X]/1 mL; SEPIA OFFICINALIS JUICE 12 [hp_X]/1 mL; SILICON DIOXIDE 12 [hp_X]/1 mL; HYDROFLUORIC ACID 30 [hp_X]/1 mL
INACTIVE INGREDIENTS: WATER; ALCOHOL

Drug Facts:

ACTIVE INGREDIENTS:

Antimonium Crudum 12X, Belladonna 12X, Calcarea Carbonica 12X, Calcarea Fluorica 12X, Calcarea Phosphorica 12X, Hekla Lava 12X, Mercurius Solubilis 12X, Plumbum Metallicum 12X, Sepia 12X, Silicea 12X, Hydrofluoricum Acidum 30X.

INDICATIONS:

For temporary relief of gum, dentition, and tooth pain.

WARNINGS:

If pregnant or breast-feeding, ask a health care professional before use.

Keep out of reach of children. In case of overdose, get medical help or contact a Poison Control Center right away.

Do not use if tamper evident seal is broken or missing.

Store in a cool, dry place.

Keep out of reach of children. In case of overdose, get medical help or contact a Poison Control Center right away.

DIRECTIONS:

10 drops orally, 3 times a day. Consult a physician for use in children under 12 years of age.

INDICATIONS:

For temporary relief of gum, dentition, and tooth pain.

INACTIVE INGREDIENTS:

Demineralized Water, 25% Ethanol

QUESTIONS:

Distributed by:

BioActive Nutritional, Inc.

1803 N. Wickham Rd.

Melbourne, FL 32935

bioactivenutritional.com

PACKAGE DISPLAY LABEL:

BioActive Homeopathic

DENTAFORCE

1 FL OZ (30 mL)